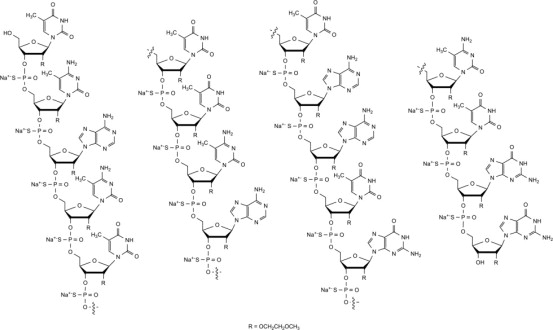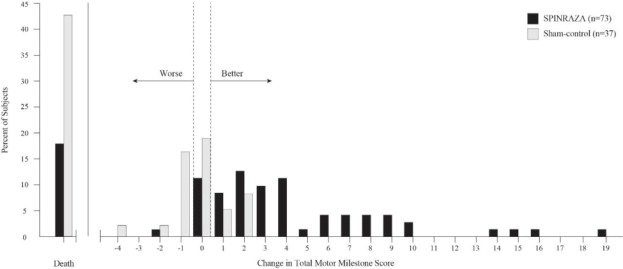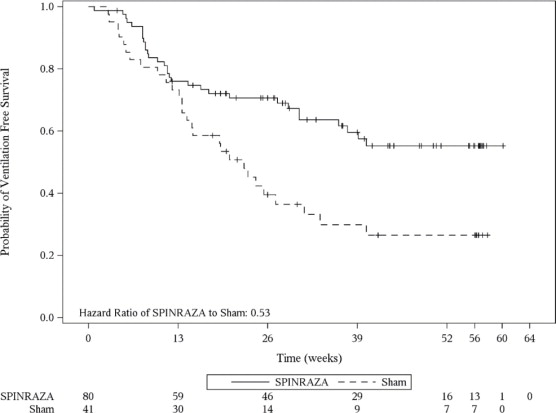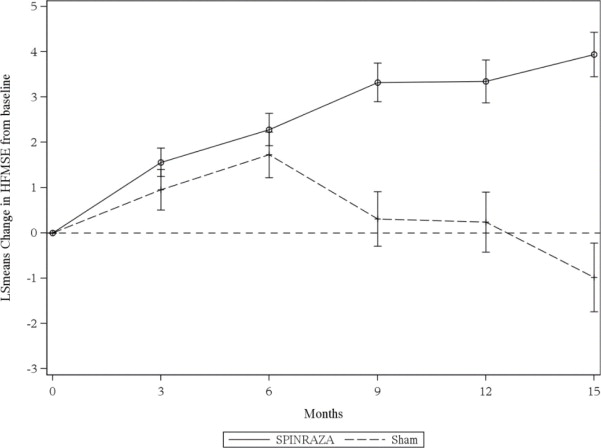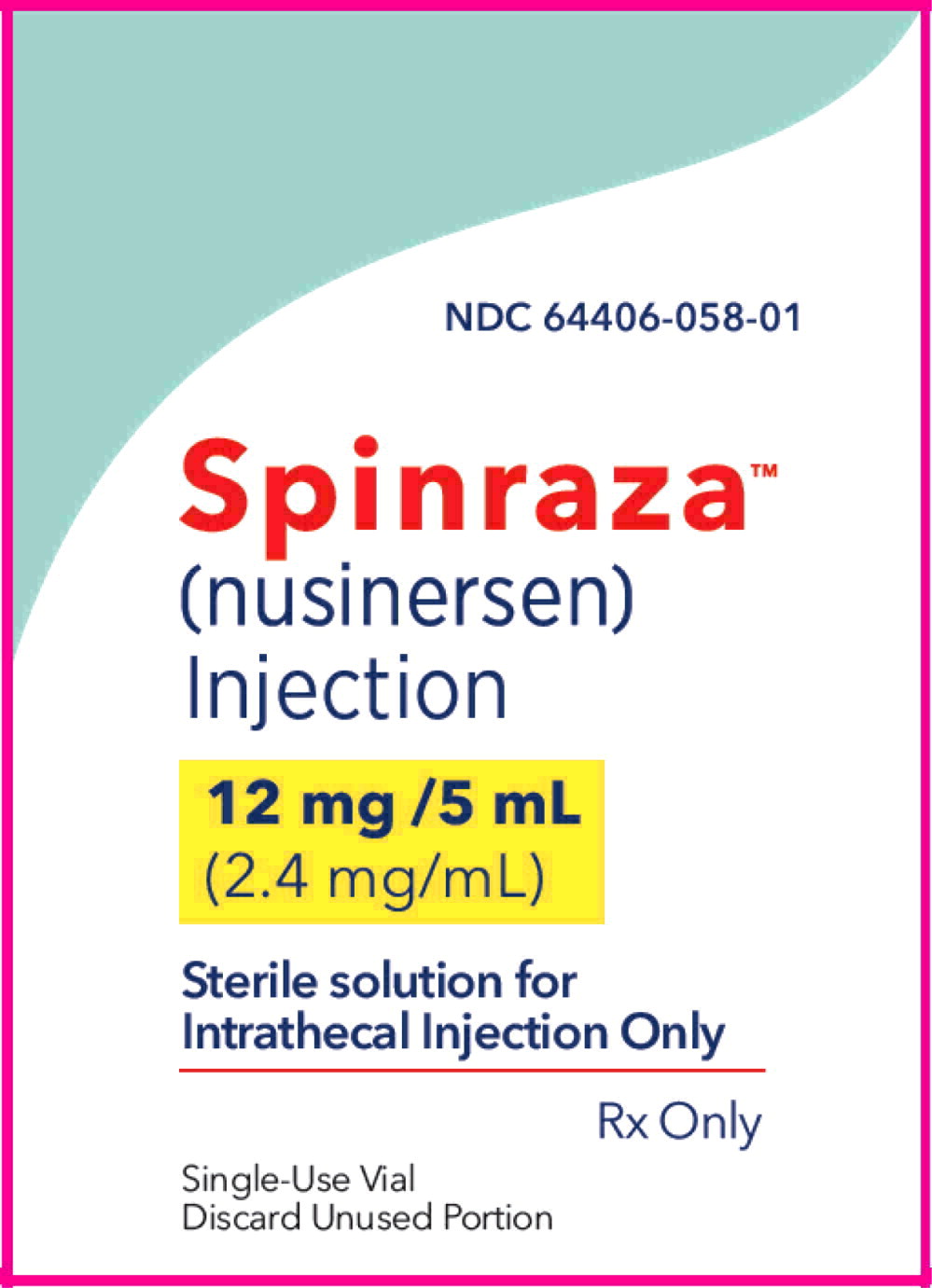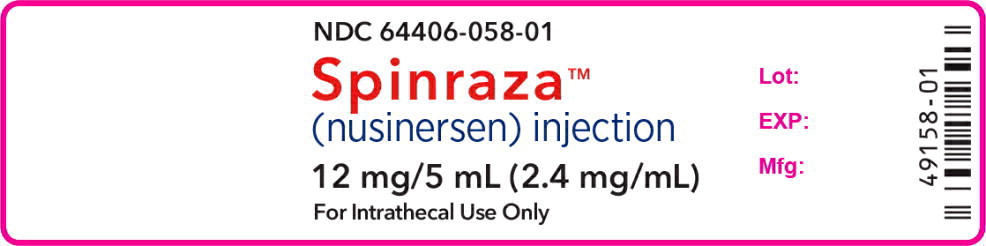 DRUG LABEL: Spinraza
NDC: 64406-058 | Form: INJECTION, SOLUTION
Manufacturer: Biogen Inc.
Category: prescription | Type: HUMAN PRESCRIPTION DRUG LABEL
Date: 20251119

ACTIVE INGREDIENTS: Nusinersen 2.4 mg/1 mL
INACTIVE INGREDIENTS: Sodium phosphate, monobasic, dihydrate 0.05 mg/1 mL; Sodium phosphate, dibasic, anhydrous 0.10 mg/1 mL; Sodium Chloride 8.77 mg/1 mL; Potassium Chloride 0.22 mg/1 mL; Calcium chloride 0.21 mg/1 mL; Magnesium chloride 0.16 mg/1 mL; Water

HIGHLIGHTS OF PRESCRIBING INFORMATION

These highlights do not include all the information needed to use
SPINRAZA® safely and effectively. See full prescribing information for SPINRAZA.
SPINRAZA (nusinersen) injection, for intrathecal use
Initial U.S. Approval: 2016

1 INDICATIONS AND USAGE

SPINRAZA is a survival motor neuron-2 (SMN2)-directed antisense oligonucleotide indicated for the treatment of spinal muscular atrophy (SMA) in pediatric and adult patients (1)

2 DOSAGE AND ADMINISTRATION

SPINRAZA is administered intrathecally (2.1)

Dosing Information (2.1)

- The recommended dosage is 12 mg (5 mL) per administration
- Initiate SPINRAZA treatment with 4 loading doses: the first three loading doses should be administered at 14-day intervals; the 4th loading dose should be administered 30 days after the 3rd dose. A maintenance dose should be administered once every 4 months thereafter.

Important Preparation and Administration Instructions (2.2)

- Allow to warm to room temperature prior to administration
- Administer within 4 hours of removal from vial
- Prior to administration, remove 5 mL of cerebrospinal fluid
- Administer as intrathecal bolus injection over 1 to 3 minutes

Laboratory Testing and Monitoring to Assess Safety (2.3)

- At baseline and prior to each dose, obtain a platelet count, coagulation laboratory testing, and quantitative spot urine protein testing

3 DOSAGE FORMS AND STRENGTHS

Injection: 12 mg/5 mL (2.4 mg/mL) in a single-dose vial (3)

4 CONTRAINDICATIONS

None.

5 WARNINGS AND PRECAUTIONS

- Thrombocytopenia and Coagulation Abnormalities: Increased risk for bleeding complications; testing required at baseline and before each dose and as clinically needed (5.1, 2.3)
- Renal Toxicity: Quantitative spot urine protein testing required at baseline and prior to each dose (5.2, 2.3)

6 ADVERSE REACTIONS

The most common adverse reactions that occurred in at least 20% of SPINRAZA-treated patients and occurred at least 5% more frequently than in control patients were:

- lower respiratory infection and constipation in patients with infantile-onset SMA (6.1)
- pyrexia, headache, vomiting, and back pain in patients with later-onset SMA (6.1)

To report SUSPECTED ADVERSE REACTIONS, contact Biogen at 1-844-477-4672 or FDA at 1-800-FDA-1088 or www.fda.gov/medwatch.

8 USE IN SPECIFIC POPULATIONS

Pregnancy: Based on animal data, may cause fetal harm (8.1)

FULL PRESCRIBING INFORMATION

1 INDICATIONS AND USAGE

SPINRAZA is indicated for the treatment of spinal muscular atrophy (SMA) in pediatric and adult patients.

2 DOSAGE AND ADMINISTRATION

2.1 Dosing Information

SPINRAZA is administered intrathecally by, or under the direction of, healthcare professionals experienced in performing lumbar punctures.

Recommended Dosage

The recommended dosage is 12 mg (5 mL) per administration.

Initiate SPINRAZA treatment with 4 loading doses. The first three loading doses should be administered at 14-day intervals. The 4th loading dose should be administered 30 days after the 3rd dose. A maintenance dose should be administered once every 4 months thereafter.

Missed Dose

Missed Loading Dose

If a loading dose (any of the 4 loading doses) is missed, administer the missed loading dose as soon as possible; adjust the date for the subsequent doses to maintain the recommended interval between doses.

Missed Maintenance Dose

Less than 8 months from last dose

Administer the missed maintenance dose as soon as possible; then administer the next maintenance dose per the originally scheduled date, as long as these two doses are administered at least 14 days apart.

At least 8 months but less than 16 months from last dose

Administer the missed maintenance dose as soon as possible, followed by one additional dose 14 days later, and then administer the next maintenance dose 4 months thereafter.

At least 16 months but less than 40 months from last dose

Administer the missed maintenance dose as soon as possible, followed by two additional doses 14 days apart, and then administer the next maintenance dose 4 months thereafter.

At least 40 months from last dose

Restart dosing as described in Recommended Dosage.

2.2 Important Preparation and Administration Instructions

SPINRAZA is for intrathecal use only.

Prepare and use SPINRAZA according to the following steps using aseptic technique. Each vial is intended for single dose only.

Preparation

- Store SPINRAZA in the carton in a refrigerator until time of use.
- Allow the SPINRAZA vial to warm to room temperature (25o C/77o F) prior to administration. Do not use external heat sources.
- Inspect the SPINRAZA vial for particulate matter and discoloration prior to administration. Do not administer SPINRAZA if visible particulates are observed or if the liquid in the vial is discolored. The use of external filters is not required.
- Withdraw 12 mg (5 mL) of SPINRAZA from the single-dose vial into a syringe and discard unused contents of the vial.
- Administer SPINRAZA within 4 hours of removal from vial.

Administration

- Consider sedation as indicated by the clinical condition of the patient.
- Consider ultrasound or other imaging techniques to guide intrathecal administration of SPINRAZA, particularly in younger patients.
- Prior to administration, remove 5 mL of cerebrospinal fluid.
- Administer SPINRAZA as an intrathecal bolus injection over 1 to 3 minutes using a spinal anesthesia needle [see Dosage and Administration (2.1)]. Do not administer SPINRAZA in areas of the skin where there are signs of infection or inflammation [see Adverse Reactions (6.3)].

2.3 Laboratory Testing and Monitoring to Assess Safety

Conduct the following laboratory tests at baseline and prior to each dose of SPINRAZA and as clinically needed [see Warnings and Precautions (5.1, 5.2)]:

- Platelet count
- Prothrombin time; activated partial thromboplastin time
- Quantitative spot urine protein testing

3 DOSAGE FORMS AND STRENGTHS

Injection: 12 mg/5 mL (2.4 mg/mL) nusinersen as a clear and colorless solution in a single-dose vial.

4 CONTRAINDICATIONS

None.

5 WARNINGS AND PRECAUTIONS

5.1 Thrombocytopenia and Coagulation Abnormalities

Coagulation abnormalities and thrombocytopenia, including acute severe thrombocytopenia, have been observed after administration of some antisense oligonucleotides.

In the sham-controlled studies for patients with infantile-onset and later-onset SMA, 24 of 146 (16%) SPINRAZA-treated patients with high, normal, or unknown platelet count at baseline developed a platelet level below the lower limit of normal, compared to 10 of 72 (14%) sham-controlled patients.

In the sham-controlled study in patients with later-onset SMA (Study 2), two SPINRAZA-treated patients developed platelet counts less than 50,000 cells per microliter, with a lowest level of 10,000 cells per microliter recorded on study day 28.

Because of the risk of thrombocytopenia and coagulation abnormalities from SPINRAZA, patients may be at increased risk of bleeding complications.

Perform a platelet count and coagulation laboratory testing at baseline and prior to each administration of SPINRAZA and as clinically needed.

5.2 Renal Toxicity

Renal toxicity, including potentially fatal glomerulonephritis, has been observed after administration of some antisense oligonucleotides.

SPINRAZA is present in and excreted by the kidney [see Clinical Pharmacology (12.3)]. In the sham-controlled studies for patients with infantile-onset and later-onset SMA, 71 of 123 (58%) of SPINRAZA-treated patients had elevated urine protein, compared to 22 of 65 (34%) sham-controlled patients. Conduct quantitative spot urine protein testing (preferably using a first morning urine specimen) at baseline and prior to each dose of SPINRAZA. For urinary protein concentration greater than 0.2 g/L, consider repeat testing and further evaluation.

6 ADVERSE REACTIONS

The following serious adverse reactions are described in detail in other sections of the labeling:

- Thrombocytopenia and Coagulation Abnormalities [see Warnings and Precautions (5.1)]
- Renal Toxicity [see Warnings and Precautions (5.2)]

6.1 Clinical Trials Experience

Because clinical trials are conducted under widely varying conditions, adverse reaction rates observed in the clinical trials of SPINRAZA cannot be directly compared to rates in clinical trials of other drugs and may not reflect the rates observed in practice.

In clinical studies, 346 patients (47% male, 76% Caucasian) were treated with SPINRAZA, including 314 exposed for at least 6 months, 258 exposed for at least 1 year, and 138 exposed for at least 2 years. The safety of SPINRAZA was studied in presymptomatic infants with SMA; pediatric patients (approximately 3 days to 16 years of age at first dose) with symptomatic SMA; in a sham-controlled trial in infants with symptomatic SMA (Study 1; n=80 for SPINRAZA, n=41 for control); in a sham-controlled trial in children with symptomatic SMA (Study 2; n=84 for SPINRAZA, n=42 for control); in an open-label study in presymptomatic infants (Study 3, n=25) and other studies in symptomatic infants (n=54) and later-onset patients (n=103). In Study 1, 58 patients were exposed for at least 6 months and 28 patients were exposed for at least 12 months. In Study 2, 84 patients were exposed for at least 6 months and 82 patients were exposed for at least 12 months.

Clinical Trial in Infantile-Onset SMA (Study 1)

In Study 1, baseline disease characteristics were largely similar in the SPINRAZA-treated patients and sham-control patients except that SPINRAZA-treated patients at baseline had a higher percentage compared to sham-control patients of paradoxical breathing (89% vs 66%), pneumonia or respiratory symptoms (35% vs 22%), swallowing or feeding difficulties (51% vs 29%), and requirement for respiratory support (26% vs 15%).

The most common adverse reactions that occurred in at least 20% of SPINRAZA-treated patients and occurred at least 5% more frequently than in control patients were lower respiratory infection and constipation. Serious adverse reactions of atelectasis were more frequent in SPINRAZA-treated patients (18%) than in control patients (10%). Because patients in Study 1 were infants, adverse reactions that are verbally reported could not be assessed in this study.

Table 1. Adverse Reactions that Occurred in at Least 5% of SPINRAZA Patients and Occurred at Least 5% More Frequently or At Least 2 Times as Frequently Than in Control Patients with Infantile-Onset SMA (Study 1)
Adverse Reactions | SPINRAZA 12 mg^1 N = 80 % | Sham-Procedure Control N = 41 %
Lower respiratory infection^2 | 55 | 37
Constipation | 35 | 22
Teething | 18 | 7
Urinary tract infection | 9 | 0
Upper respiratory tract congestion | 8 | 2
Ear infection | 6 | 2
Flatulence | 5 | 2
Decreased weight | 5 | 2
^1 Loading doses followed by 12 mg (5 mL) once every 4 months
^2 Includes adenovirus infection, bronchiolitis, bronchitis, bronchitis viral, corona virus infection, Influenza, lower respiratory tract infection, lower respiratory tract infection viral, lung infection, parainfluenzae virus infection, pneumonia, pneumonia bacterial, pneumonia influenzal, pneumonia moraxella, pneumonia parainfluenzae viral, pneumonia pneumococcal, pneumonia pseudomonal, pneumonia respiratory syncytial viral, pneumonia viral, and respiratory syncytial virus bronchiolitis.

In an open-label clinical study in infants with symptomatic SMA, severe hyponatremia was reported in a patient treated with SPINRAZA requiring salt supplementation for 14 months.

Cases of rash were reported in patients treated with SPINRAZA. One patient, 8 months after starting SPINRAZA treatment, developed painless red macular lesions on the forearm, leg, and foot over an 8-week period. The lesions ulcerated and scabbed over within 4 weeks, and resolved over several months. A second patient developed red macular skin lesions on the cheek and hand ten months after the start of SPINRAZA treatment, which resolved over 3 months. Both cases continued to receive SPINRAZA and had spontaneous resolution of the rash.

SPINRAZA may cause a reduction in growth as measured by height when administered to infants, as suggested by observations from the controlled study. It is unknown whether any effect of SPINRAZA on growth would be reversible with cessation of treatment.

Clinical Trial in Later-Onset SMA (Study 2)

In Study 2, baseline disease characteristics were largely similar in the SPINRAZA-treated patients and sham-control patients except for the proportion of SPINRAZA-treated patients who had ever achieved the ability to stand without support (13% vs 29%) or walk with support (24% vs 33%).

The most common adverse reactions that occurred in at least 20% of SPINRAZA-treated patients and occurred at least 5% more frequently than in control patients were pyrexia, headache, vomiting, and back pain.

Table 2. Adverse Reactions that Occurred in at Least 5% of SPINRAZA Patients and Occurred at Least 5% More Frequently or At Least 2 Times as Frequently Than in Control Patients with Later-Onset SMA (Study 2)
Adverse Reactions | SPINRAZA 12 mg^1 N=84 % | Sham-Procedure Control N=42 %
Pyrexia | 43 | 36
Headache | 29 | 7
Vomiting | 29 | 12
Back pain | 25 | 0
Epistaxis | 7 | 0
Fall | 5 | 0
Respiratory tract congestion | 5 | 2
Seasonal allergy | 5 | 2
^1 Loading doses followed by 12 mg (5 mL) once every 6 months

Post-lumbar puncture syndrome has also been observed after administration of SPINRAZA.

6.2 Immunogenicity

As with all oligonucleotides, there is potential for immunogenicity. The detection of antibody formation is highly dependent on the sensitivity and specificity of the assay. Additionally, the observed incidence of antibody (including neutralizing antibody) positivity in an assay may be influenced by several factors, including assay methodology, sample handling, timing of sample collection, concomitant medications, and underlying disease. For these reasons, comparison of the incidence of antibodies to nusinersen in the studies described below with the incidence of antibodies in other studies or to other products may be misleading.

The immunogenic response to nusinersen was evaluated in 294 patients with post-baseline plasma samples for anti-drug antibodies (ADAs). Seventeen patients (6%) developed treatment-emergent ADAs, of which 5 were transient, 12 were considered to be persistent. Persistent was defined as having one positive test followed by another one more than 100 days after the first positive test. In addition, “persistent” is also defined as having one or more positive samples and no sample more than 100 days after the first positive sample. Transient was defined as having one or more positive results and not confirmed to be persistent. There are insufficient data to evaluate an effect of ADAs on clinical response, adverse events, or the pharmacokinetic profile of nusinersen.

6.3 Postmarketing Experience

The following adverse reactions have been identified during post-approval use of SPINRAZA. Because these reactions are reported voluntarily from a population of uncertain size, it is not always possible to reliably estimate their frequency or establish a causal relationship to drug exposure.

Serious infections associated with lumbar puncture, such as meningitis, have been reported. Hydrocephalus, aseptic meningitis, hypersensitivity reactions (e.g. angioedema, urticaria, rash), and arachnoiditis have also been reported.

8 USE IN SPECIFIC POPULATIONS

8.1 Pregnancy

Risk Summary

There are no adequate data on the developmental risk associated with the use of SPINRAZA in pregnant women. When nusinersen was administered by subcutaneous injection to mice throughout pregnancy and lactation, developmental toxicity (long-term neurobehavioral impairment) was observed at all doses tested (see Data). In the U.S. general population, the estimated background risk of major birth defects and miscarriage in clinically recognized pregnancies is 2 to 4% and 15 to 20%, respectively. The background risk of major birth defects and miscarriage for the indicated population is unknown.

Data

Animal Data

When nusinersen (0, 3, 10, or 25 mg/kg) was administered subcutaneously to male and female mice every other day prior to and during mating and continuing in females throughout organogenesis, no adverse effects on embryofetal development were observed. Subcutaneous administration of nusinersen (0, 6, 12.6, or 25 mg/kg) to pregnant rabbits every other day throughout organogenesis produced no evidence of embryofetal developmental toxicity.

When nusinersen (1.4, 5.8, or 17.2 mg/kg) was administered to pregnant female mice by subcutaneous injection every other day throughout organogenesis and continuing once every six days throughout the lactation period, adverse neurobehavioral effects (alterations in locomotor activity, learning and memory deficits) were observed when offspring were tested after weaning or as adults. A no-effect level for neurobehavioral impairment was not established.

8.2 Lactation

Risk Summary

There are no data on the presence of nusinersen in human milk, the effects on the breastfed infant, or the effects of the drug on milk production.Nusinersen was detected in the milk of lactating mice when administered by subcutaneous injection. The developmental and health benefits of breastfeeding should be considered along with the mother's clinical need for SPINRAZA and any potential adverse effects on the breastfed infant from SPINRAZA or from the underlying maternal condition.

8.4 Pediatric Use

The safety and effectiveness of SPINRAZA in pediatric patients from newborn to 17 years have been established [see Clinical Studies (14.1)].

Juvenile Animal Toxicity Data

In intrathecal toxicity studies in juvenile monkeys, administration of nusinersen (0, 0.3, 1, or 3 mg/dose for 14 weeks and 0, 0.3, 1, or 4 mg/dose for 53 weeks) resulted in brain histopathology (neuronal vacuolation and necrosis/cellular debris in the hippocampus) at the mid and high doses and acute, transient deficits in lower spinal reflexes at the high dose in each study. In addition, possible neurobehavioral deficits were observed on a learning and memory test at the high dose in the 53-week monkey study. The no-effect dose for neurohistopathology in monkeys (0.3 mg/dose) is approximately equivalent to the human dose when calculated on a yearly basis and corrected for the species difference in CSF volume.

8.5 Geriatric Use

Clinical studies of SPINRAZA did not include sufficient numbers of subjects aged 65 and over to determine whether they respond differently from younger subjects.

11 DESCRIPTION

Nusinersen is a modified antisense oligonucleotide, where the 2'-hydroxy groups of the ribofuranosyl rings are replaced with 2'-O-2-methoxyethyl groups and the phosphate linkages are replaced with phosphorothioate linkages. Nusinersen binds to a specific sequence in the intron downstream of exon 7 of the SMN2 transcript. The structural formula is:

SPINRAZA is supplied as a sterile, preservative-free, colorless solution for intrathecal use in a single-dose glass vial. Each 1 mL solution contains 2.4 mg of nusinersen (equivalent to 2.53 mg of nusinersen sodium salt). Each 1 mL also contains calcium chloride dihydrate (0.21 mg) USP, magnesium chloride hexahydrate (0.16 mg) USP, potassium chloride (0.22 mg) USP, sodium chloride (8.77 mg) USP, sodium phosphate dibasic anhydrous (0.10 mg) USP, sodium phosphate monobasic dihydrate (0.05 mg) USP, and Water for Injection USP. The product may contain hydrochloric acid or sodium hydroxide to adjust pH. The pH is ~7.2.

The molecular formula of SPINRAZA is C234H323N61O128P17S17Na17 and the molecular weight is 7501.0 daltons.

12 CLINICAL PHARMACOLOGY

12.1 Mechanism of Action

SPINRAZA is an antisense oligonucleotide (ASO) designed to treat SMA caused by mutations in chromosome 5q that lead to SMN protein deficiency. Using in vitro assays and studies in transgenic animal models of SMA, SPINRAZA was shown to increase exon 7 inclusion in SMN2 messenger ribonucleic acid (mRNA) transcripts and production of full-length SMN protein.

12.2 Pharmacodynamics

Autopsy samples from patients (n=3) had higher levels of SMN2 messenger ribonucleic acid (mRNA) containing exon 7 in the thoracic spinal cord compared to untreated SMA infants.

Cardiac Electrophysiology

Across the sham-controlled studies in 247 patients with spinal muscular atrophy who received either SPINRAZA or sham-control, QTcF values >500 ms and change from baseline values >60 ms were observed in 4 (2.4%) patients receiving SPINRAZA. Compared to the sham-control, there was no increase in the incidence of cardiac adverse reactions associated with delayed ventricular repolarization in patients treated with SPINRAZA.

12.3 Pharmacokinetics

Absorption

Intrathecal injection of SPINRAZA into the cerebrospinal fluid (CSF) allows nusinersen to be distributed from the CSF to the target central nervous system (CNS) tissues. Following intrathecal administration, trough plasma concentrations of nusinersen were relatively low, compared to the trough CSF concentration. Median plasma Tmax values ranged from 1.7 to 6.0 hours. Mean plasma Cmax and AUC values increased approximately dose-proportionally up to a dose of 12 mg.

Distribution

Autopsy data from patients (n=3) showed that SPINRAZA administered intrathecally was distributed within the CNS and peripheral tissues, such as skeletal muscle, liver, and kidney.

Elimination

Metabolism

Nusinersen is metabolized via exonuclease (3'- and 5')-mediated hydrolysis and is not a substrate for, or inhibitor or inducer of CYP450 enzymes.

Excretion

The mean terminal elimination half-life is estimated to be 135 to 177 days in CSF, and 63 to 87 days in plasma. The primary route of elimination is likely by urinary excretion for nusinersen and its chain-shortened metabolites. At 24 hours, only 0.5% of the administered dose was recovered in the urine.

13 NONCLINICAL TOXICOLOGY

13.1 Carcinogenesis, Mutagenesis, Impairment of Fertility

Carcinogenesis

Administration of nusinersen (0, 5, 15, or 50 mg/kg) to male and female mice by subcutaneous injection, once every two weeks for 2 years, resulted in an increase in the incidence of vascular tumors (combined hemangioma and hemangiosarcoma) at the highest dose tested.

Mutagenesis

Nusinersen demonstrated no evidence of genotoxicity in in vitro (Ames and chromosomal aberration in CHO cells) and in vivo (mouse micronucleus) assays.

Impairment of Fertility

When nusinersen (0, 3, 10, or 25 mg/kg) was administered by subcutaneous injection to mice every other day prior to and during mating and continuing in females throughout organogenesis, no adverse effects on male or female fertility were observed.

14 CLINICAL STUDIES

The efficacy of SPINRAZA was demonstrated in two double-blind, sham-procedure controlled clinical trials in symptomatic infantile-onset and later-onset SMA patients (Study 1 and Study 2) and was supported by open-label clinical trials conducted in presymptomatic and symptomatic SMA patients. The overall findings from these trials support the effectiveness of SPINRAZA across the range of SMA patients, and appear to support the early initiation of treatment with SPINRAZA.

14.1 Infantile-Onset SMA

Study 1 (NCT02193074) was a multicenter, randomized, double-blind, sham-procedure controlled study in 121 symptomatic infants ≤ 7 months of age at the time of first dose, diagnosed with SMA (symptom onset before 6 months of age). Patients were randomized 2:1 to receive either 12 mg SPINRAZA or sham injection as a series of loading doses administered intrathecally followed by maintenance doses administered every 4 months. Patients in this study were deemed most likely to develop Type 1 SMA.

A planned interim efficacy analysis was conducted based on patients who died, withdrew, or completed at least 183 days of treatment. Of the 82 patients included in the interim analysis (52 patients in the SPINRAZA-treated group and 30 in the sham-control group), 44% were male, 87% were Caucasian, 2% were Black, and 4% were Asian. Age at first treatment ranged from 30 to 262 days (median 181). Length of treatment ranged from 6 to 442 days (median 261 days). Baseline demographics were balanced between the SPINRAZA and control groups with the exception of age at first treatment (median age 175 vs. 206 days, respectively). The SPINRAZA and control groups were balanced with respect to gestational age, birth weight, disease duration, and SMN2 copy number. Median disease duration was 14 weeks. There was some imbalance in age at symptom onset with 88% of subjects in the SPINRAZA group and 77% in the control group experiencing symptoms within the first 12 weeks of life.

The primary endpoint assessed at the time of interim analysis was the proportion of responders: patients with an improvement in motor milestones according to Section 2 of the Hammersmith Infant Neurologic Exam (HINE). This endpoint evaluates seven different areas of motor milestone development, with a maximum score between 2-4 points for each, depending on the milestone, and a total maximum score of 26. A treatment responder was defined as any patient with at least a 2-point increase (or maximal score of 4) in ability to kick (consistent with improvement by at least 2 milestones), or at least a 1-point increase in the motor milestones of head control, rolling, sitting, crawling, standing or walking (consistent with improvement by at least 1 milestone). To be classified as a responder, patients needed to exhibit improvement in more categories of motor milestones than worsening. Of the 82 patients who were eligible for the interim analysis, a statistically significantly greater percentage of patients achieved the definition of a motor milestone responder in the SPINRAZA group (40%) compared to the sham-control group (0%). Results from the final analysis were consistent with those from the interim analysis (Table 3). Fifty-one percent of patients in the SPINRAZA group achieved the definition of a motor milestone responder compared to 0% of patients in the sham-control group. Figure 1 is a descriptive display of the distribution of net change from baseline in the total motor milestone score for Section 2 of the HINE for patients in the final efficacy set who did not die or withdraw from the study.

The primary endpoint assessed at the final analysis was time to death or permanent ventilation (≥ 16 hours ventilation/day continuously for > 21 days in the absence of an acute reversible event or tracheostomy). Statistically significant effects on event-free survival and overall survival were observed in patients in the SPINRAZA group compared to those in the sham-control group (Table 4). A 47% reduction in the risk of death or permanent ventilation was observed in the SPINRAZA group (p=0.005) (Figure 2). Median time to death or permanent ventilation was not reached in SPINRAZA group and was 22.6 weeks in the sham-control group. A statistically significant 63% reduction in the risk of death was also observed (p=0.004).

At the final analysis, the study also assessed treatment effects on the Children's Hospital of Philadelphia Infant Test of Neuromuscular Disorders (CHOP-INTEND), which is an evaluation of motor skills in patients with infantile-onset SMA. The CHOP-INTEND results are displayed in Table 3.

Table 3. Motor Milestone Response and CHOP-INTEND Results of the Final Analysis of Patients with Infantile-Onset SMA (Study 1)
Endpoint | SPINRAZA-treated Patients (n=73) | Sham-control Patients (n=37)
Motor function
Motor milestones^1 Proportion achieving pre-defined motor milestone responder criteria (HINE section 2)^2,3 | 37 (51%) P<0.0001 | 0 (0%)
CHOP-INTEND^1 Proportion achieving a 4-point improvement Proportion achieving a 4-point worsening^4 | 52 (71%) p<0.0001 2 (3%) | 1 (3%) 17 (46%)
^1At the final analysis, CHOP-INTEND and motor milestone analyses were conducted using the Efficacy Set (SPINRAZA n=73; Sham-control n=37).
^2Assessed at the later of Day 183, Day 302, and Day 394 Study Visit
^3According to HINE section 2: ≥2 point increase [or maximal score] in ability to kick, OR ≥1 point increase in the motor milestones of head control, rolling, sitting, crawling, standing or walking, AND improvement in more categories of motor milestones than worsening), defined as a responder for this primary analysis.
^4Not statistically controlled for multiple comparisons

Table 4. Survival Results of Patients with Infantile-Onset SMA (Study 1)
Endpoint | SPINRAZA-treated Patients (n=80) | Sham-control Patients (n=41)
Survival
Event-free survival^1 Number of patients who died or received permanent ventilation Hazard ratio (95% CI) p-value^2 | 31 (39%) | 28 (68%)
Event-free survival^1 Number of patients who died or received permanent ventilation Hazard ratio (95% CI) p-value^2 | 0.53 (0.32 -0.89) p=0.005
Overall survival^1 Number of patients who died | 13 (16%) | 16 (39%)
Hazard Ratio (95% CI) p-value^2 | 0.37 (0.18 – 0.77) p=0.004
^1At the final analysis, event-free survival and overall survival were assessed using the Intent to Treat population (ITT SPINRAZA n=80; Sham-control n=41).
^2Based on log-rank test stratified by disease duration

Figure 1. Percent of Patients Who Died and Net Change from Baseline in Total Motor Milestone Score (HINE) Among Patients Alive in the Final Efficacy Set of Study 1 *

*For subjects who were alive and ongoing in the study, the change in total motor milestone score was calculated at the later of Day 183, Day 302, or Day 394.

Figure 2. Event-Free Survival in the Intent to Treat Set

14.2 Later-Onset SMA

Study 2 (NCT02292537) was a multicenter, randomized, double-blind, sham-procedure controlled study in 126 symptomatic children with later-onset SMA (symptom onset after 6 months of age). Patients were randomized 2:1 to either SPINRAZA 12 mg or sham injection as a series of loading doses administered intrathecally followed by maintenance doses administered every 6 months.

The median age at screening was 3 years (range 2-9 years), and the median age of onset of clinical signs and symptoms of SMA was 11 months (range 6-20 months). Of the 126 patients included in the study, 47% were male, 75% were Caucasian, 2% were Black, and 18% were Asian. Length of treatment ranged from 324 to 482 days (median 450 days). At baseline, patients had a mean Hammersmith Functional Motor Scale – Expanded (HFMSE) score of 21.6, all had achieved independent sitting, and no patients had achieved independent walking. Patients in this study were deemed most likely to develop Type 2 or 3 SMA.

The primary endpoint assessed was the change from baseline score at Month 15 on the HFMSE. The HFMSE evaluates motor function in patients with SMA who have limited ambulation, comprising of 33 scored activities that give objective information on motor ability and clinical progression, such as the ability to sit unassisted, stand, or walk. Each item is scored from 0-2, with a maximum total score of 66. Higher scores indicate better motor function. The primary analysis was conducted in the Intent to Treat (ITT) population, which included all subjects who were randomized and received at least 1 dose of SPINRAZA or at least one sham procedure. At the final analysis, a statistically significant improvement in HFMSE scores from baseline to Month 15 was observed in the SPINRAZA-treated group compared to the sham-control group (Table 5).

Table 5. HFMSE Results in Patients with Later-Onset SMA (Study 2)
Endpoint | SPINRAZA-treated Patients (n=84) | Sham-control Patients (n=42)
HFMSE score Change from baseline in total HFMSE score at 15 months^1,2,3 Proportion of patients who achieved at least a 3-point improvement from baseline to Month 15^1 | 3.9 (95% CI: 3.0, 4.9) p=0.0000001 56.8% (95% CI: 45.6, 68.1) p=0.0006^4 | -1.0 (95% CI: -2.5, 0.5) 26.3% (95% CI: 12.4, 40.2)
^1Assessed using the Intent to Treat population who received at least one dose of SPINRAZA or at least one sham procedure (SPINRAZA n=84; Sham-control n=42); data for patients without a Month 15 visit were imputed using the multiple imputation method
^2Least squares mean
^3Negative value indicates worsening, positive value indicates improvement.
^4Based on logistic regression with treatment effect and adjustment for each subject's age at screening and HFMSE score at baseline

Figure 3. Mean Change from Baseline in HFMSE Score Over Time in the Intent to Treat Set^(1, 2) (Study 2)

^1Data for patients without a Month 15 visit were imputed using the multiple imputation method

^2Error bars denote +/- standard error

14.3 Presymptomatic SMA

The results of the sham-controlled trial in infantile-onset (Study 1) (NCT02193074) and later-onset (Study 2) (NCT02292537) SMA patients were supported by an open-label uncontrolled trial conducted in 25 presymptomatic SMA patients who had a genetic diagnosis of 5q SMA and 2 or 3 copies of SMN2 (Study 3) (NCT02386553). In Study 3, 15 patients (60%) who had 2 SMN2 copies, and 10 patients (40%) who had 3 SMN2 copies; 48% were male, 56% were Caucasian, 12% were Asian, 4% were American Indian or Alaska Native, and 28% were of another race, or had no race reported. Patients ranged in age from 3 days to 42 days (median 22 days) at the time of first dose. Patients received 12 mg SPINRAZA as a series of loading doses administered intrathecally, followed by maintenance doses administered every 4 months. Patients were assessed with the World Health Organization (WHO) motor milestones, a set of 6 milestones in motor development that would be expected to be attained by 24 months of age in healthy children. An interim analysis was performed after all patients had received SPINRAZA for at least 14 months (median 25 months, range 14 to 34 months). Patients ranged in age from 14 to 34 months (median age of 26 months) at the time of the analysis. At the time of the interim analysis (data cutoff May 2018), all patients receiving SPINRAZA before the onset of SMA symptoms survived without requiring permanent ventilation, and beyond what would be expected based on their SMN2 copy number. All 25 patients (100%) had achieved the WHO motor milestone of sitting without support, and 22 patients (88%) had achieved the milestone of walking with assistance. Of the 22 patients who were older than the age expected to have achieved the ability to walk independently (as defined by the 95th percentile of the WHO expected age of achievement), 17 (77%) achieved the milestone of walking alone (i.e., walking independently).

16 HOW SUPPLIED/STORAGE AND HANDLING

16.1 How Supplied

SPINRAZA injection is a sterile, clear and colorless solution supplied as a 12 mg/5 mL (2.4 mg/mL) solution in a single-dose glass vial free of preservatives. The NDC is 64406-058-01.

16.2 Storage and Handling

Store in a refrigerator between 2°C to 8°C (36°F to 46°F) in the original carton to protect from light. Do not freeze.

SPINRAZA should be protected from light and kept in the original carton until time of use.

If no refrigeration is available, SPINRAZA may be stored in its original carton, protected from light at or below 30oC (86oF) for up to 14 days.

Prior to administration, unopened vials of SPINRAZA can be removed from and returned to the refrigerator, if necessary. If removed from the original carton, the total combined time out of refrigeration should not exceed 30 hours at a temperature that does not exceed 25oC (77oF).

17 PATIENT COUNSELING INFORMATION

Thrombocytopenia and Coagulation Abnormalities

Inform patients and caregivers that SPINRAZA could increase the risk of bleeding. Inform patients and caregivers of the importance of obtaining blood laboratory testing at baseline and prior to each dose to monitor for signs of increased potential for bleeding. Instruct patients and caregivers to seek medical attention if unexpected bleeding occurs [see Warnings and Precautions (5.1)].

Renal Toxicity

Inform patients and caregivers that SPINRAZA could cause renal toxicity. Inform patients and caregivers of the importance of obtaining urine testing at baseline and prior to each dose to monitor for signs of potential renal toxicity [see Warnings and Precautions (5.2)].

49655-10

Manufactured for:
Biogen
Cambridge, MA 02142
SPINRAZA is a registered trademark of Biogen.
© Biogen 2016-2024

Principal Display Panel - Spinraza 12mg/5ml Carton Label

NDC 64406-058-01

Spinraza™

(nusinersen)

Injection

12 mg/5 mL

(2.4 mg/mL)

Sterile solution for
Intrathecal Injection Only

Rx Only

Single Use Vial

Discard Unused Portion

Principal Display Panel - Spinraza 12mg/5ml Vial Label

NDC 64406-058-01

Spinraza™

(nusinersen) injection

12 mg/5 mL (2.4 mg/mL)

For Intrathecal Injection Only